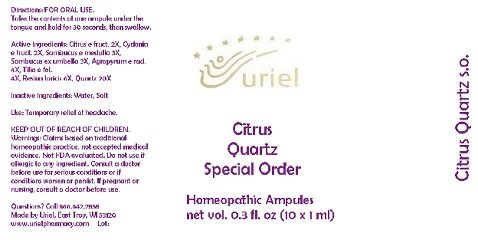 DRUG LABEL: Citrus Quartz Special Order
NDC: 48951-3194 | Form: LIQUID
Manufacturer: Uriel Pharmacy Inc.
Category: homeopathic | Type: HUMAN OTC DRUG LABEL
Date: 20180522

ACTIVE INGREDIENTS: LEMON 2 [hp_X]/1 mL; QUINCE 2 [hp_X]/1 mL; SAMBUCUS NIGRA FLOWERING TOP 3 [hp_X]/1 mL; ELYMUS REPENS ROOT 4 [hp_X]/1 mL; LINDEN LEAF 4 [hp_X]/1 mL; LARIX DECIDUA RESIN 6 [hp_X]/1 mL; SILICON DIOXIDE 6 [hp_X]/1 mL
INACTIVE INGREDIENTS: WATER; SODIUM CHLORIDE

Citrus Quartz Special Order

INDICATIONS AND USAGE

Directions: FOR ORAL USE.

DOSAGE AND ADMINISTRATION

Take the contents of one ampule under the tongue and hold for 30 seconds, then swallow.

ACTIVE INGREDIENT

Active Ingredients: Citrus e fruct. 2X, Cydonia e fruct. 2X, Sambucus e medulla 3X, Sambucus ex umbella 3X, Agropyrum e rad. 4X, Tilia e fol. 4X, Resina laricis 6X, Quartz 20X

Inactive Ingredients: Water, Salt

PURPOSE

Use: Temporary relief of headache.

KEEP OUT OF REACH OF CHILDREN.

WARNINGS

Warnings: Claims based on traditional homeopathic practice, not accepted medical evidence. Not FDA evaluated. Do not use if allergic to any ingredient. Consult a doctor before use for serious conditions or if conditions worsen or persist. If pregnant or nursing, consult a doctor before use.

QUESTIONS

Questions? Call 866.642.2858 Made by Uriel, East Troy, WI 53120 www.urielpharmacy.com